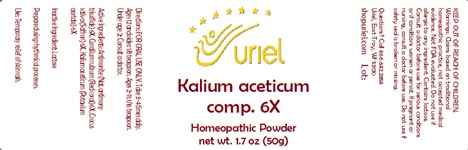 DRUG LABEL: Kalium aceticum comp. 6
NDC: 48951-6004 | Form: POWDER
Manufacturer: Uriel Pharmacy Inc.
Category: homeopathic | Type: HUMAN OTC DRUG LABEL
Date: 20241211

ACTIVE INGREDIENTS: CORALLIUM RUBRUM EXOSKELETON 6 [hp_X]/1 g; SAFFRON 6 [hp_X]/1 g; POTASSIUM ACETATE 6 [hp_X]/1 g; ANTIMONY TRISULFIDE 6 [hp_X]/1 g
INACTIVE INGREDIENTS: LACTOSE

Kalium aceticum comp. 6

INDICATIONS AND USAGE

Directions: FOR ORAL USE ONLY.

DOSAGE AND ADMINISTRATION

Take 3-4 times daily. Ages 12 and older: 1/8 teaspoon. Ages 2-11: 1/16 teaspoon. Under age 2: Consult a doctor.

ACTIVE INGREDIENT

Active Ingredients: Antimonite (Nat. antimony trisulfide) 6X, Corallium rubrum (Red coral) 6X, Crocus sativa (Saffron) 6X, Kalium aceticum (Potassium acetate) 6X

Inactive Ingredient: Lactose

Prepared using rhythmical processes.

PURPOSE

Use: Temporary relief of skin rash.

KEEP OUT OF REACH OF CHILDREN.

WARNINGS

Warnings: Claims based on traditional homeopathic practice, not accepted medical evidence. Not FDA evaluated. Do not use if allergic to any ingredient. Contains lactose. Consult a doctor before use for serious conditions or if conditions worsen or persist. If pregnant or nursing, consult a doctor before use. Do not use if safety seal is broken or missing.

QUESTIONS

Questions? Call 866.642.2858 Uriel, East Troy, WI 53120 shopuriel.com Lot: